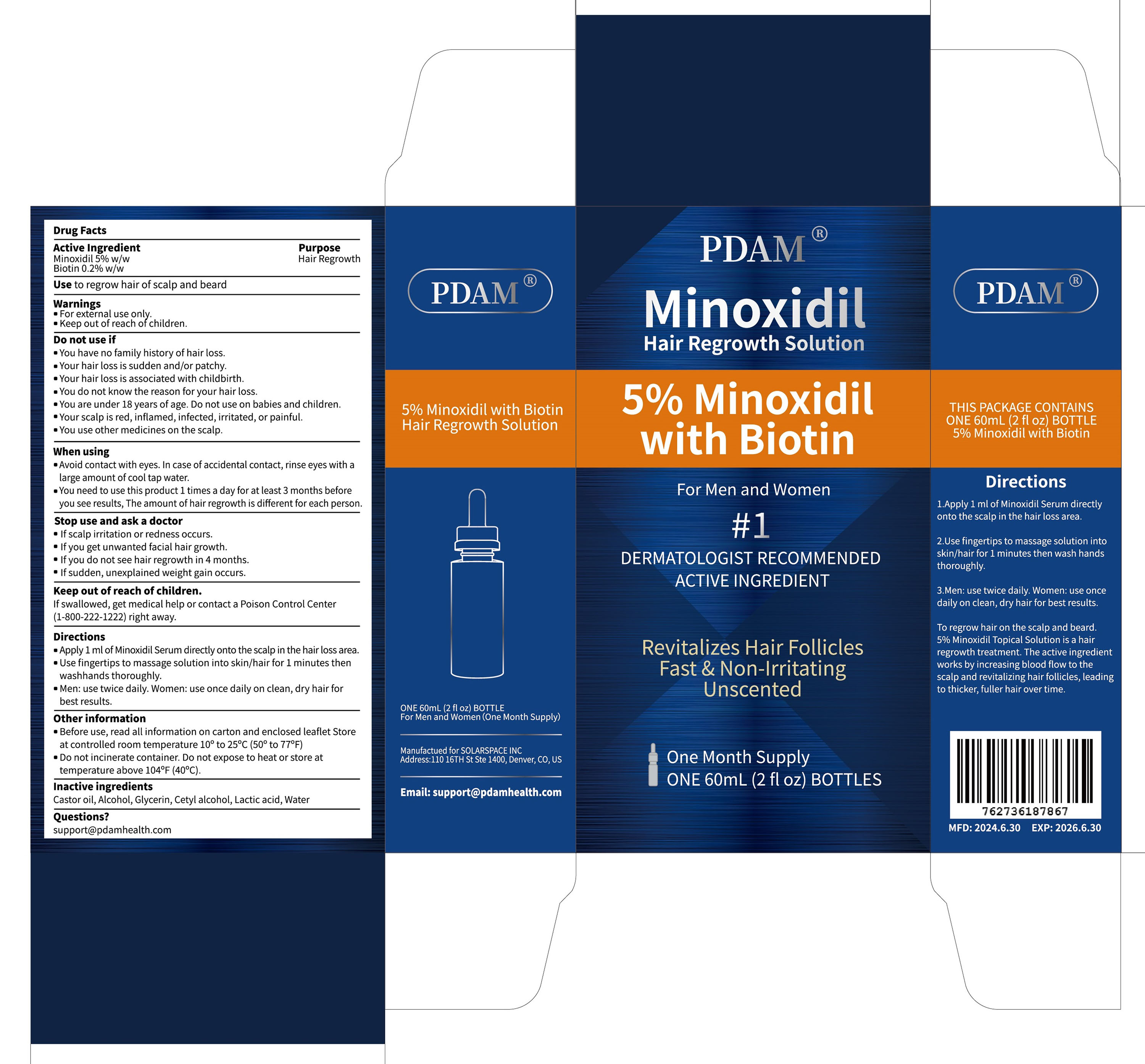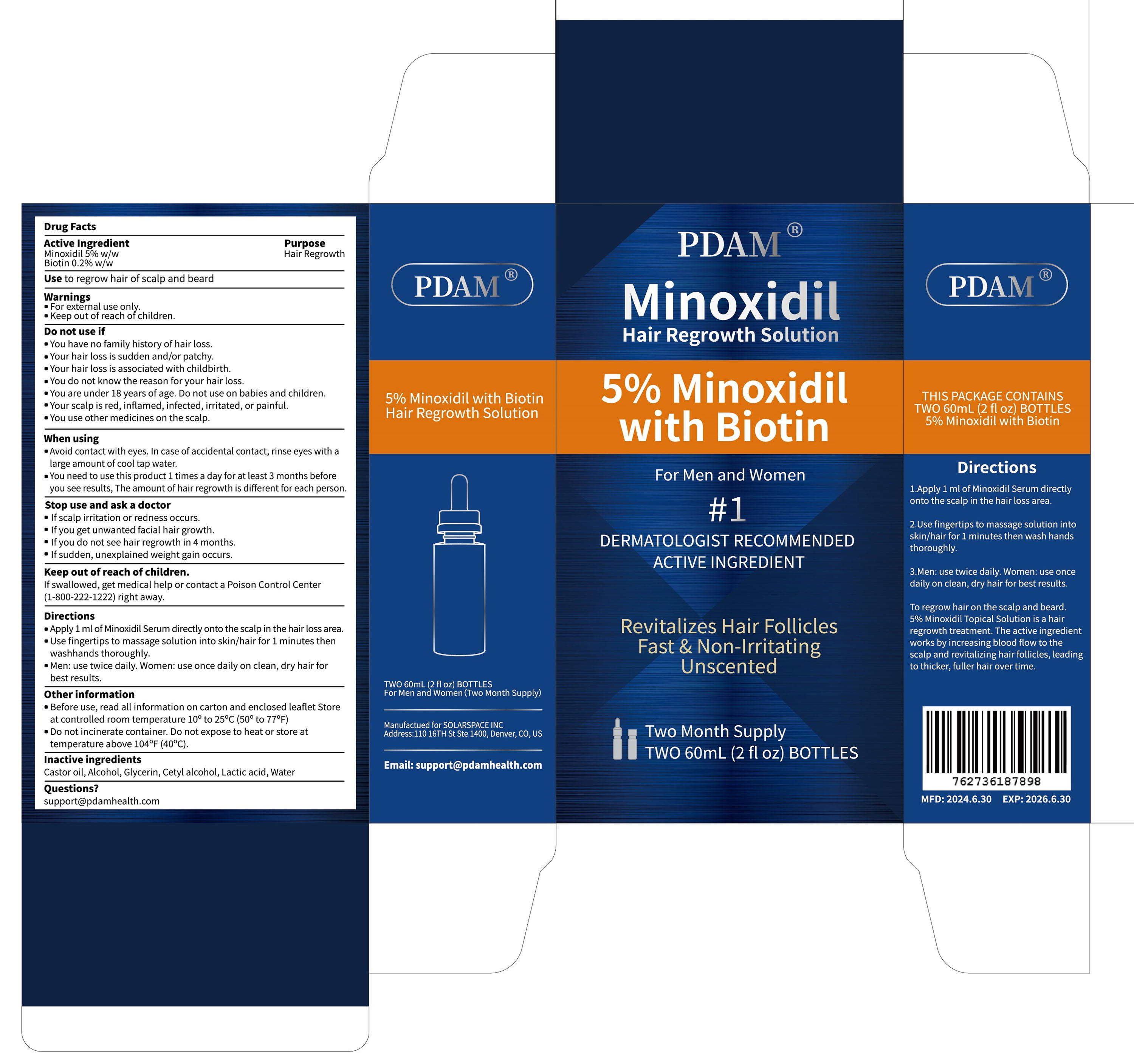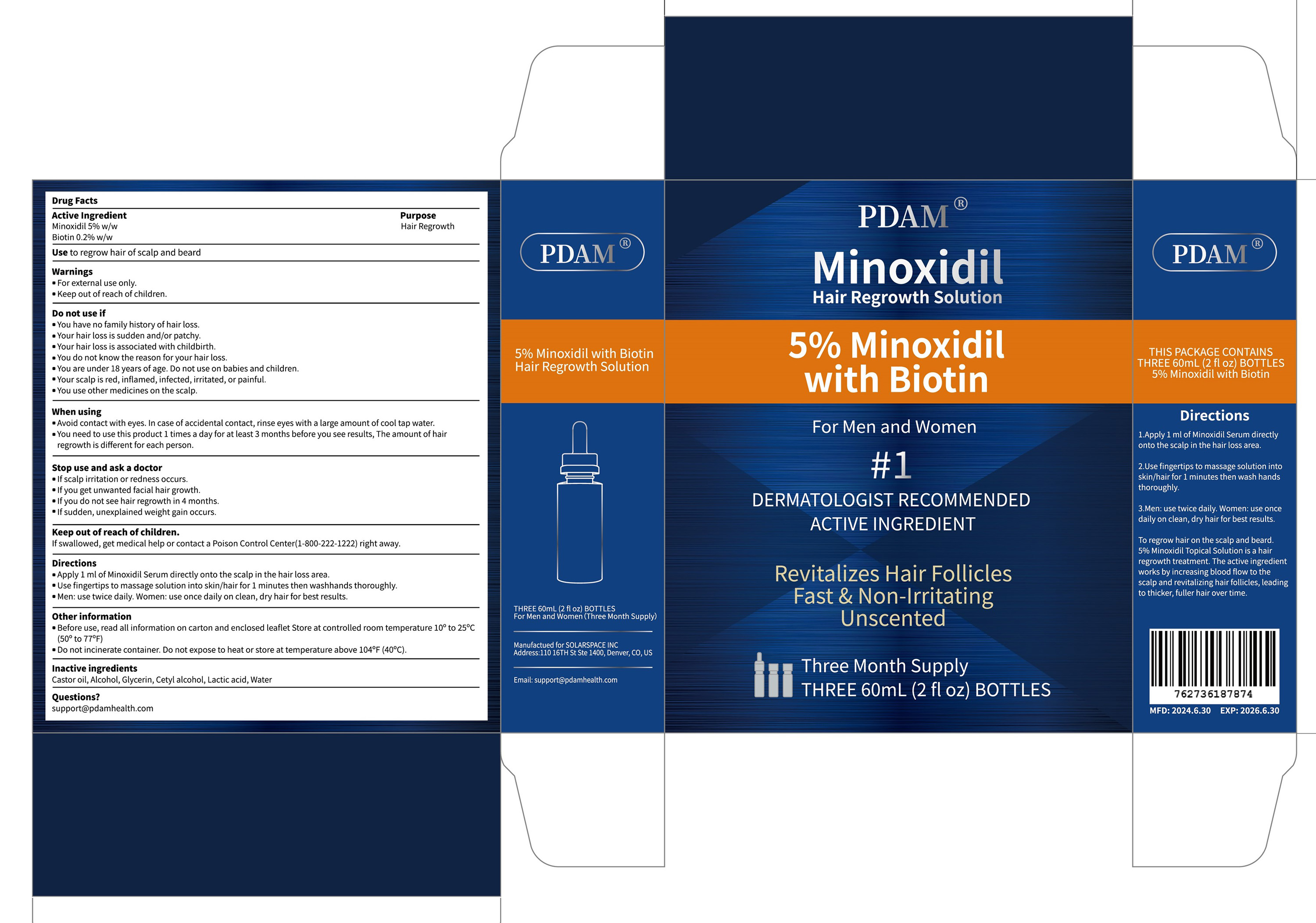 DRUG LABEL: 5% Minoxidil Hair Regrowth Solution With Biotin
NDC: 83767-301 | Form: SOLUTION
Manufacturer: Guangzhou Ruijiu Electronic Technology Co., Ltd.
Category: otc | Type: HUMAN OTC DRUG LABEL
Date: 20240725

ACTIVE INGREDIENTS: MINOXIDIL 5 g/100 g; BIOTIN 0.2 g/100 g
INACTIVE INGREDIENTS: WATER; ALCOHOL; LACTIC ACID; CASTOR OIL; GLYCERIN; CETYL ALCOHOL

5% Minoxidil Hair Regrowth Solution With Biotin

5% Minoxidil Hair Regrowth Solution With Biotin

ACTIVE INGREDIENT

Minoxidil 5%
Biotin 0.2%

PURPOSE

Hair Regrowth

INDICATIONS AND USAGE

Use to regrow hair of scalp and beard

WARNINGS

For external use only.
Keep out of reach of children.

DO NOT USE

You have no family history of hair loss.
Your hair loss is sudden and/or patchy.
Your hair loss is associated with childbirth.
You do not know the reason for your hair loss.
You are under 18 years of age. Do not use on babies and children
Your scalp is red,inflamed, infected, irritated, or painful.
You use other medicines on the scalp.

WHEN USING

Avoid contact with eyes. In case of accidental contact, rinse eyes with alarge amount of cool tap water.
You need to use this product 1 times a day for at least 3 months beforeyou see results, The amount of hair regrowth is different for each person.

STOP USE

Ifscalp irritation or redness occurs.
lf you get unwanted facial hair growth.
lf you do not see hair regrowth in 4 months.
lf sudden, unexplained weight gain occurs.

KEEP OUT OF REACH OF CHILDREN

lf swallowed, get medical help or contact a Poison Control Center
(1-800-222-1222)right away.

DOSAGE AND ADMINISTRATION

Apply 1 ml of Minoxidil Serum directly onto the scalp in the hair loss area.
Use fingertips to massage solution into skin/hair for 1 minutes thenwashhands thoroughly.
Men: use twice daily.Women: use once daily on clean, dry hair for best results.

STORAGE AND HANDLING

Before use, read all information on carton and enclosed leaflet Storeat controlled room temperature 10° to 25°C (50° to 77°F)
Do not incinerate container. Do not expose to heat or store attemperature above 104°F(40°C).

INACTIVE INGREDIENT

CASTOR OIL
ALCOHOL
GLYCERIN
CETYL ALCOHOL
LACTIC ACID
WATER